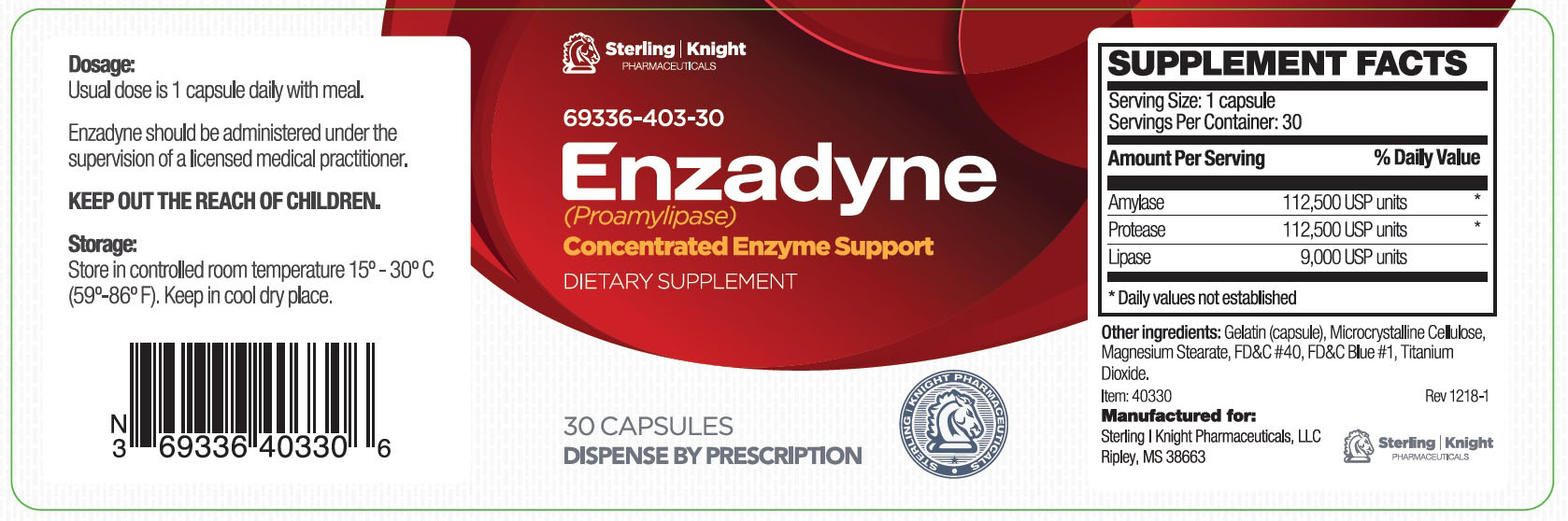 DRUG LABEL: Enzadyne
NDC: 69336-403 | Form: CAPSULE
Manufacturer: Sterling Knight Pharmaceuticals LLC
Category: other | Type: Dietary Supplement
Date: 20190618

ACTIVE INGREDIENTS: PANCRELIPASE AMYLASE 112500 [USP'U]/1 1; PANCRELIPASE PROTEASE 112500 [USP'U]/1 1; PANCRELIPASE LIPASE 9000 [USP'U]/1 1
INACTIVE INGREDIENTS: GELATIN; MICROCRYSTALLINE CELLULOSE; MAGNESIUM STEARATE; FD&C RED NO. 40; FD&C BLUE NO. 1; TITANIUM DIOXIDE

Enzadyne Capsules
Dietary Supplement

HEALTH CLAIM:

Enzadyne Capsules Dietary Supplemement

Dispensed by Prescription†

DESCRIPTION:

Enzadyne is an orally administered prescription digestive enzyme formulation for the clinical dietary management of suboptimal nutritional status in patients where advanced supplementation is required and nutritional supplementation in physiologically stressful conditions for maintenance of good health is needed.

Enzadyne should be administered under the supervision of a licensed medical practitioner.

INDICATIONS AND USAGE:
Enzadyne is an orally administered prescription digestive enzyme formulation for the clinical dietary management of suboptimal nutritional status in patients where advanced supplementation is required and nutritional supplementation in physiologically stressful conditions for maintenance of good health is needed.

WARNINGS AND PRECAUTIONS:

This product is contraindicated in patients with a known hypersensitivity to any of the ingredients.

Enzadyne should only be used under the direction and supervision of a licensed medical practitioner. Use with caution in patients that may have a medical condition, are pregnant, lactating, trying to conceive, under the age of 18, or taking medications.

DOSAGE AND ADMINISTRATION:

Usual adult dose is 1 capsule daily with or without food. Do not exceed 3 capsules per day.

STORAGE:

Store at controlled room temperature 15°-30°C (59°F-86°F). Keep in cool dry place. Call your doctor about side effects. You may report side effects to FDA at 1-800-FDA-1088. KEEP THIS OUT OF THE REACH OF CHILDREN.

PACKAGE LABEL:

Reserved for Professional Recommendation

All prescriptions using this product shall be pursuant to state statutes as applicable. This is not an Orange Book product. This product may be administered only under a physician’s supervision. There are no implied or explicit claims on therapeutic equivalence.

Manufactured for:

Sterling-Knight Pharmaceuticals, LLC

Ripley, MS 38663